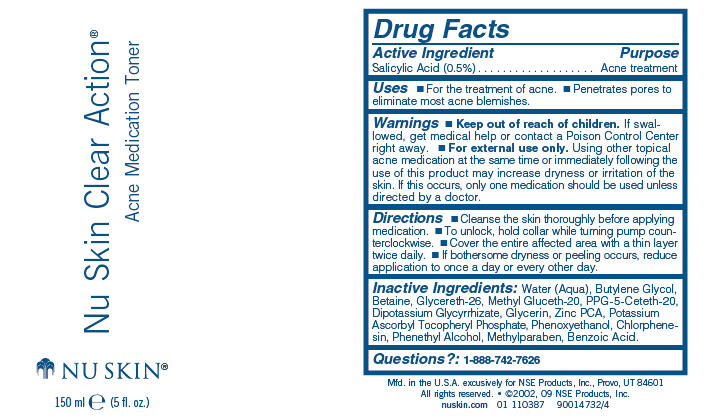 DRUG LABEL: Nu Skin Clear Action
NDC: 62839-0138 | Form: LIQUID
Manufacturer: NSE Products, Inc.
Category: otc | Type: HUMAN OTC DRUG LABEL
Date: 20241230

ACTIVE INGREDIENTS: Salicylic Acid 5 mg/1 mL
INACTIVE INGREDIENTS: Water; Butylene Glycol; Betaine; Glycereth-26; Methyl Gluceth-20; PPG-5-Ceteth-20; Glycerin; Zinc Pidolate; Phenoxyethanol; Chlorphenesin; Phenylethyl Alcohol; Methylparaben; Benzoic Acid

Nu Skin Clear Action®
Acne Medication Toner

Drug Facts

Active Ingredient

Salicylic Acid (0.5%)

Purpose

Acne treatment

Uses

- For the treatment of acne.
- Penetrates pores to eliminate most acne blemishes.

Warnings

- Keep out of reach of children. If swallowed, get medical help or contact a Poison Control Center right away.

WHEN USING

- For external use only. Using other topical acne medication at the same time or immediately following the use of this product may increase dryness or irritation of the skin. If this occurs, only one medication should be used unless directed by a doctor.

Directions

- Cleanse the skin thoroughly before applying medication.
- To unlock, hold collar while turning pump counterclockwise.
- Cover the entire affected area with a thin layer twice daily.
- If bothersome dryness or peeling occurs, reduce application to once a day or every other day.

Inactive Ingredients

Water (Aqua), Butylene Glycol, Betaine, Glycereth-26, Methyl Gluceth-20, PPG-5-Ceteth-20, Dipotassium Glycyrrhizate, Glycerin, Zinc PCA, Potassium Ascorbyl Tocopheryl Phosphate, Phenoxyethanol, Chlorphenesin, Phenethyl Alcohol, Methylparaben, Benzoic Acid.

Questions?

1-888-742-7626

PRINCIPAL DISPLAY PANEL - 150 ml Bottle Label

Nu Skin Clear Action®

Acne Medication Toner

NU SKIN®

150 ml e (5 fl. oz.)